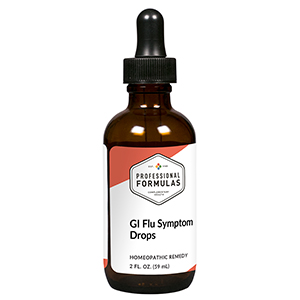 DRUG LABEL: GI Flu Symptom Drops
NDC: 63083-2088 | Form: LIQUID
Manufacturer: Professional Complementary Health Formulas
Category: homeopathic | Type: HUMAN OTC DRUG LABEL
Date: 20190815

ACTIVE INGREDIENTS: ARTEMISIA ANNUA FLOWERING TOP 1 [hp_X]/59 mL; MARRUBIUM VULGARE WHOLE 1 [hp_X]/59 mL; LEMON JUICE 2 [hp_X]/59 mL; LAVANDULA ANGUSTIFOLIA SUBSP. ANGUSTIFOLIA FLOWERING TOP 2 [hp_X]/59 mL; MENTHA X PIPERITA WHOLE 2 [hp_X]/59 mL; BASIL 2 [hp_X]/59 mL; POPULUS BALSAMIFERA LEAF BUD 2 [hp_X]/59 mL; POGOSTEMON CABLIN TOP 3 [hp_X]/59 mL; IPECAC 6 [hp_X]/59 mL; COMFREY ROOT 6 [hp_X]/59 mL; HAEMOPHILUS INFLUENZAE 12 [hp_X]/59 mL
INACTIVE INGREDIENTS: ALCOHOL; WATER

C88

ACTIVE INGREDIENTS

Chamomilla 1X
Marrubium vulgare 1X
Citrus limonum 2X
Lavandula officinalis 2X
Mentha piperita 2X
Ocimum basilicum 2X
Populus candicans 2X
Pogostemon cablin 3X
Ipecacuanha 6X
Symphytum officinale 6X
Influenzinum 12X

QUESTIONS

Professional Formulas

PO Box 2034 Lake Oswego, OR 97035

INDICATIONS

For the temporary relief of diarrhea, mild abdominal cramping or pain, nausea or vomiting, occasional headache, or muscle aches.*

PURPOSE

*Claims based on traditional homeopathic practice, not accepted medical evidence. Not FDA evaluated.

WARNINGS

Persistent symptoms may be a sign of a serious condition. If symptoms persist or are accompanied by a fever, rash, or persistent headache, consult a doctor. Keep out of the reach of children. In case of overdose, get medical help or contact a poison control center right away. If pregnant or breastfeeding, ask a healthcare professional before use.

Keep out of the reach of children.

PREGNANCY OR BREAST FEEDING

If pregnant or breastfeeding, ask a healthcare professional before use.

DIRECTIONS

Place drops under tongue 30 minutes before/after meals. Adults and children 12 years and over: Take 10 drops up to 3 times per day for up to 6 weeks. For immediate onset of symptoms, take 10 to 15 drops every 15 minutes up to 3 hours. For less severe symptoms, take 10-15 drops hourly up to 8 hours. Consult a physician for use in children under 12 years of age.

OTHER INFORMATION

Tamper resistant. If seal is broken, do not use. After opening, close container tightly and store at room temperature away from heat.

INACTIVE INGREDIENTS

20% ethanol, purified water.

LABEL

Est 1985

Professional Formulas

Complementary Health

GI Flu Symptom Drops

Homeopathic Remedy

2 FL. OZ. (59 mL)